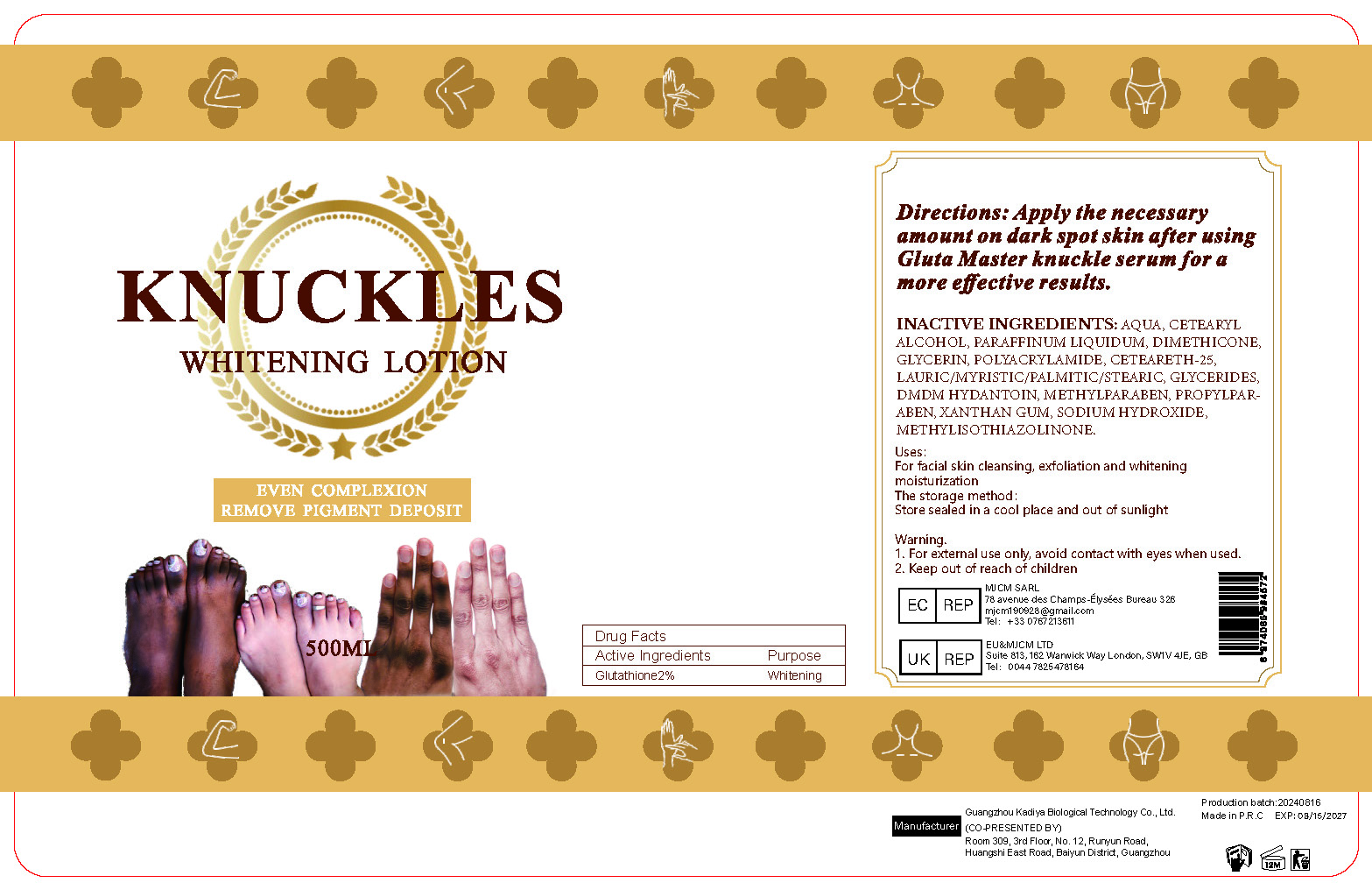 DRUG LABEL: Knuckle WhiteningLotion
NDC: 84423-044 | Form: EMULSION
Manufacturer: Guangzhou Kadiya Biotechnology Co., Ltd.
Category: otc | Type: HUMAN OTC DRUG LABEL
Date: 20240828

ACTIVE INGREDIENTS: GLUTATHIONE 10 mg/500 mL
INACTIVE INGREDIENTS: CETOSTEARYL ALCOHOL; DMDM HYDANTOIN; GLYCERIN; POLYACRYLAMIDE (10000 MW); PROPYLPARABEN; MINERAL OIL; SODIUM HYDROXIDE; DIMETHICONE; METHYLPARABEN; XANTHAN GUM; WATER; CETEARETH-25; METHYLISOTHIAZOLINONE

PURPOSE

For facial skin cleansing, exfoliation and whitening moisturization

INACTIVE INGREDIENT

AQUA、CETEARYL ALCOHOL、PARAFFINUM LIQUIDUM、DIMETHICONE、GLYCERIN、POLYACRYLAMIDE、CETEARETH-25、LAURIC/MYRISTIC/PALMITIC/STEARIC、GLYCERIDES、DMDM HYDANTOIN、METHYLPARABEN、PROPYLPARABEN、XANTHAN GUM、SODIUM HYDROXIDE、 METHYLISOTHIAZOLINONE

WARNINGS

1、For external use only, avoid contact with eyes when used
2、Keep out of reach of children

INDICATIONS AND USAGE

Apply the necessary amount on dark spot skin after using Gluta Master knuckle serum for a more effective results.

DOSAGE AND ADMINISTRATION

Apply the necessary amount on dark spot skin after using Gluta Master knuckle serum for a more effective results.

KEEP OUT OF REACH OF CHILDREN SECTION

Active Ingredients
Glutathione2%

PACKAGE LABEL

Active Ingredients
Glutathione2%

Uses：
For facial skin cleansing, exfoliation and whitening moisturization
The storage method：
Store sealed in a cool place and out of sunlight

Warning.
1、For external use only, avoid contact with eyes when used
2、Keep out of reach of children

Inactive ingredients：
AQUA、CETEARYL ALCOHOL、PARAFFINUM LIQUIDUM、DIMETHICONE、GLYCERIN、POLYACRYLAMIDE、CETEARETH-25、LAURIC/MYRISTIC/PALMITIC/STEARIC、GLYCERIDES、DMDM HYDANTOIN、METHYLPARABEN、PROPYLPARABEN、XANTHAN GUM、SODIUM HYDROXIDE、 METHYLISOTHIAZOLINONE